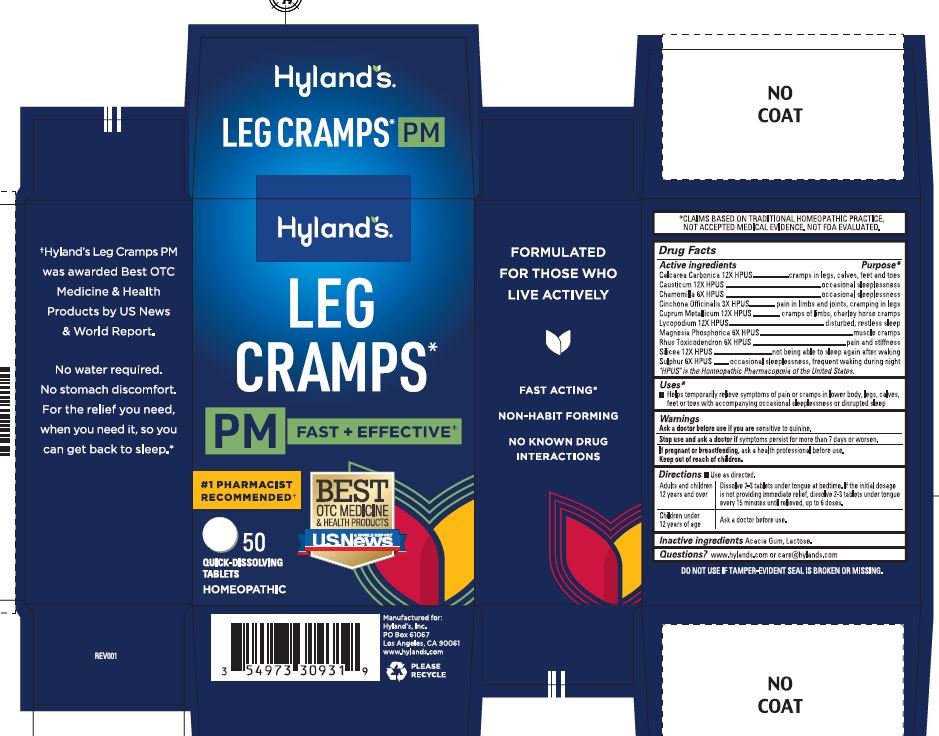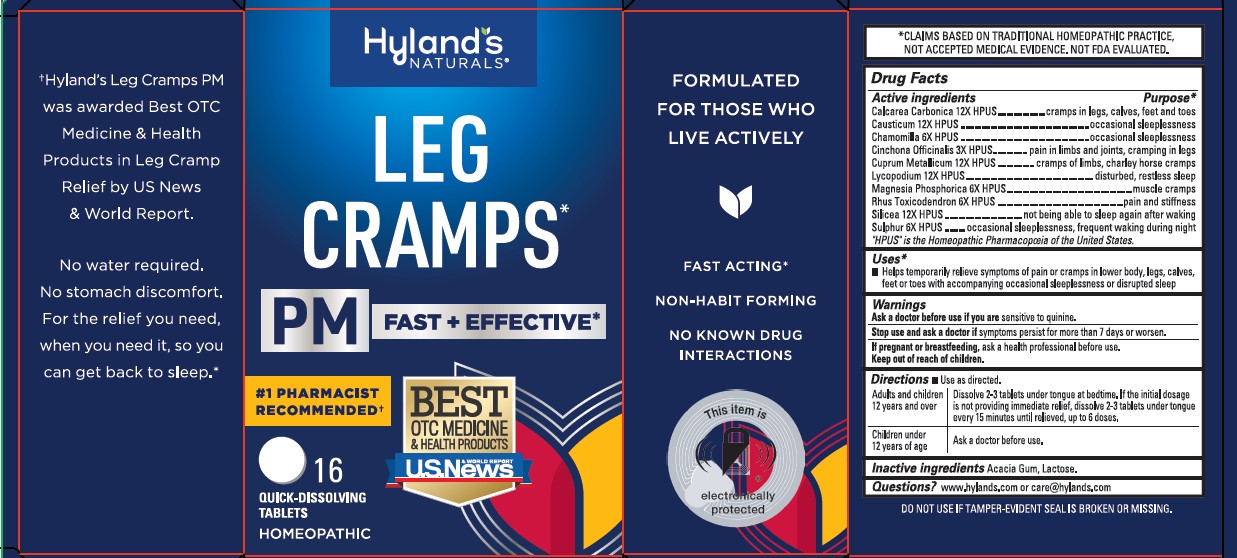 DRUG LABEL: Leg Cramps PM
NDC: 54973-3093 | Form: TABLET, SOLUBLE
Manufacturer: Hyland's Inc.
Category: homeopathic | Type: HUMAN OTC DRUG LABEL
Date: 20250109

ACTIVE INGREDIENTS: OYSTER SHELL CALCIUM CARBONATE, CRUDE 12 [hp_X]/1 1; CAUSTICUM 12 [hp_X]/1 1; MATRICARIA RECUTITA 6 [hp_X]/1 1; CINCHONA OFFICINALIS BARK 3 [hp_X]/1 1; COPPER 12 [hp_X]/1 1; LYCOPODIUM CLAVATUM SPORE 12 [hp_X]/1 1; MAGNESIUM PHOSPHATE, DIBASIC TRIHYDRATE 6 [hp_X]/1 1; TOXICODENDRON PUBESCENS LEAF 6 [hp_X]/1 1; SILICON DIOXIDE 12 [hp_X]/1 1; SULFUR 6 [hp_X]/1 1
INACTIVE INGREDIENTS: LACTOSE; ACACIA

Hyland's Leg Cramps PM

Purpose

Temporarily relieves the symptoms of pain and cramps in lower body, legs, calves, feet and toes with accompanying occasional sleeplessness and disrupted sleep.

Drug Facts

Active ingredients

Active Ingredients | Purpose*
Calcarea Carbonica 12X HPUS | cramps in legs, calves, feet and toes
Causticum 12X HPUS | occasional sleeplessness
Chamomilla 6X HPUS | occasional sleeplessness
Cinchona Officinalis 3X HPUS | pain in limbs and joints; cramping in legs
Cuprum Metallicum 12X HPUS | cramps of limbs, charley horse cramps
Lycopodium 12X HPUS | disturbed, restless sleep
Magnesia Phosphorica 6X HPUS | muscle cramps
Rhus Toxicodendron 6X HPUS | pain and stiffness
Silicea 12X HPUS | not being able to sleep again after waking
Sulphur 6X HPUS | occasional sleeplessness, frequent waking during night

“HPUS” indicates that the active ingredients are in the official Homeopathic Pharmacopœia of the United States.

Uses*

■ Helps temporarily relieve symptoms of pain or cramps in lower body, legs, calves, feet or toes with accompanying occasional sleeplessness or disrupted sleep

Warnings

Ask a doctor before use if you are

sensitive to quinine.

Stop use and ask a doctor if

symptoms persist for more than 7 days or worsen.

If pregnant or breastfeeding

Ask a health professional before use.

Directions

■ Use as directed.

Adults and children; 12 years and over | Dissolve 2-3 tablets under tongue at bedtime. If the initial dosage is not providing immediate relief, dissolve 2-3 tablets under tongue every 15 minutes until relieved, up to 6 doses.
Children under 12 years of age | Ask a doctor before use.

Inactive Ingredients

Acacia Gum, Lactose.

Questions?

www.hylands.com or care@hylands.com

Indications and Usage Dosage and Administration

Updated Usesto:Temporarily relieves the symptoms of pain or cramps in lower body, legs, calves,

feet or toes with accompanying occasional sleeplessness or disrupted sleep

Updated Directionsto:

Adults and children; 12 years and over | Dissolve 2-3 tablets under tongue before bedtime.; If the initial dosage is not providing relief, dissolve 2-3; tablets under tongue every 15 minutes, up to 6 doses.
Under 12 years of age | Consult a physician.

Indications and Usage

Uses section...updated to "Helps temporarily relieve symptoms of pain or cramps in lower body, legs, calves, feet or toes with accompanying occasional sleeplessness or disrupted sleep"

Indications and Usage

Added asterisk (*) to Uses

Principal Display Panel

Hyland's

NATURALS

LEG CRAMPS

PM FAST + EFFECTIVE*

#1 PHARMACIST

RECOMENDED

BEST

OTC MEDICINE

& HEALTH PRODUCTS

& WORLD REPORT

U.S. News

50

QUICK-DISSOLVING

TABLETS

HOMEOPATHIC